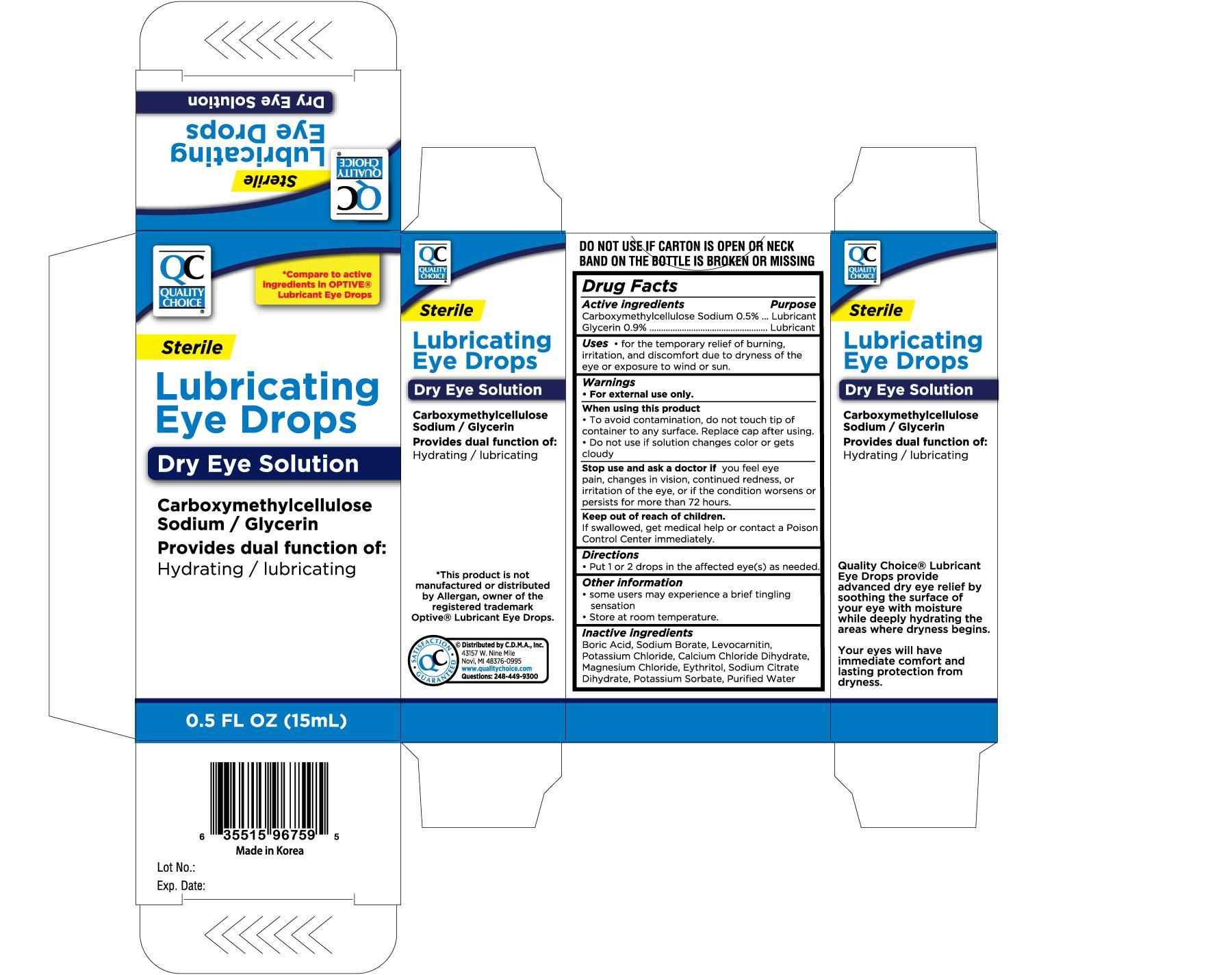 DRUG LABEL: QUALITY CHOICE LUBRICATING EYE DROPS
NDC: 63868-969 | Form: SOLUTION
Manufacturer: CHAIN DRUG MARKETING ASSOCIATION INC
Category: otc | Type: HUMAN OTC DRUG LABEL
Date: 20120930

ACTIVE INGREDIENTS: CARBOXYMETHYLCELLULOSE SODIUM 5 mg/1 mL; GLYCERIN 9 mg/1 mL
INACTIVE INGREDIENTS: BORIC ACID; SODIUM BORATE; LEVOCARNITINE; POTASSIUM CHLORIDE; CALCIUM CHLORIDE; MAGNESIUM CHLORIDE; ERYTHRITOL; TRISODIUM CITRATE DIHYDRATE; WATER

Drug Facts

ACTIVE INGREDIENT

Active ingredients------------------------------------------------Purpose

Carboxymethylcellulose Sodium 0.5%-------------------Lubricant

Glycerin 0.9%-----------------------------------------------------Lubricant

Uses

- For the temporary relief of burning, irritation and discomfort due to dryness of the eye or from irritation from wind or sun.

Warnings

- For external use only

When using this product

- To avoid contamination, do not touch tip of container to any surface. Replace cap after using.
- Do not use if solution changes color or gets cloudy.

Stop use and ask a doctor if

You feel eye pain, changes in vision, continued redness, or irritation of the eye, or if the condition worsens or persists for more than 72 hours.

Keep out of reach of children.

If swallowed, get medical help or contact a Poison Control Center immediately.

Directions

Put 1 or 2 drops in the affected eye/s as needed.

Other information

- some users may experience a brief tingling sensation
- Store at room temperature.

Inactive ingredients:

Boric Acid, Sodium Borate, Levocarnitin, Potassium Chloride, Calcium Chloride Dihydrate, Magnesium Chloride, Erythritol, Sodium Citrate Dihydrate, Potassium Sorbate, Purified Water

DOSAGE AND ADMINISTRATION

Distributed by C.D.M.A., Inc.

43157 W. Nine Mile

Novi, MI 48376-0995

www.qualitychoice.com

Made in Korea